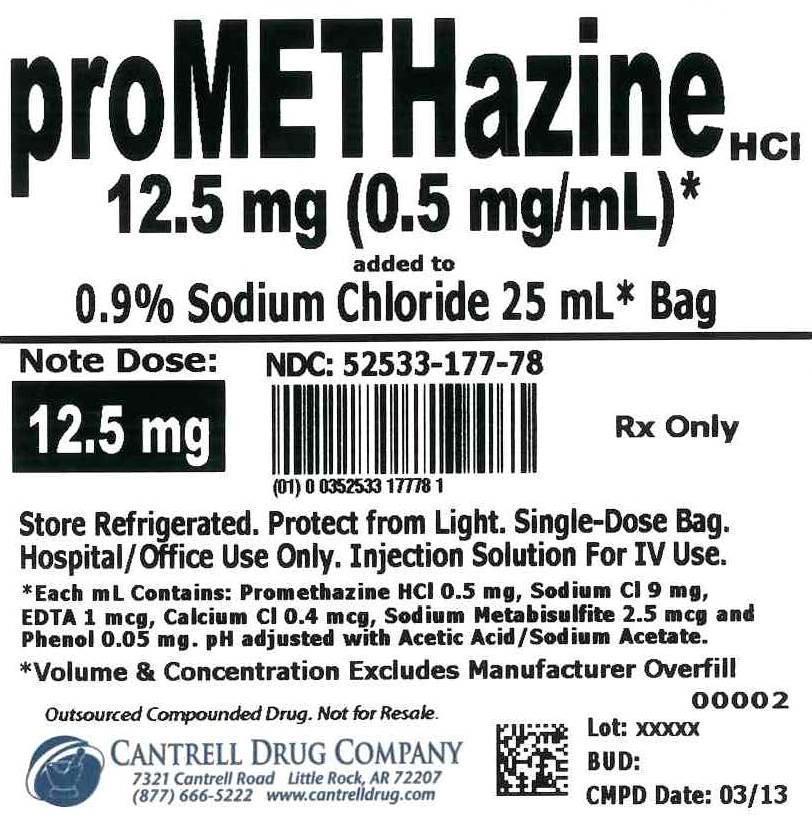 DRUG LABEL: Promethazine HCl
NDC: 52533-177 | Form: INJECTION, SOLUTION
Manufacturer: Cantrell Drug Company
Category: prescription | Type: HUMAN PRESCRIPTION DRUG LABEL
Date: 20140813

ACTIVE INGREDIENTS: PROMETHAZINE HYDROCHLORIDE 0.5 mg/1 mL
INACTIVE INGREDIENTS: SODIUM CHLORIDE 9 mg/1 mL; EDETATE SODIUM 0.025 mg/1 mL; CALCIUM CHLORIDE 0.01 mg/1 mL; SODIUM METABISULFITE 0.0625 mg/1 mL; PHENOL 1.25 mg/1 mL; WATER

Promethazine HCl 12.5 mg Added to 0.9% Sodium Chloride 25 mL Bag